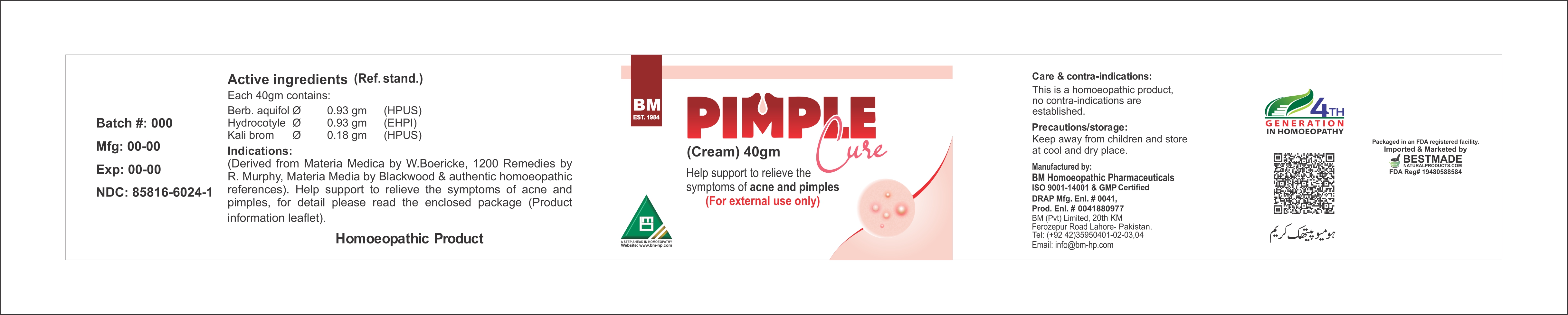 DRUG LABEL: BM Pimples Cure
NDC: 85816-6024 | Form: CREAM
Manufacturer: BM Private Limited
Category: homeopathic | Type: HUMAN OTC DRUG LABEL
Date: 20260212

ACTIVE INGREDIENTS: BERBERIS AQUIFOLIUM ROOT BARK 1 [hp_X]/1 g; CENTELLA ASIATICA WHOLE 1 [hp_X]/1 g; POTASSIUM BROMIDE 1 [hp_X]/1 g; ZINC OXIDE 0.0165 g/1 g
INACTIVE INGREDIENTS: BEESWAX 0.0178 g/1 g; WATER 0.715 g/1 g; TRIETHANOLAMINE 0.014 g/1 g; PROPYLPARABEN SODIUM 0.0007 g/1 g; STEARIC ACID 0.0725 g/1 g; TALC 0.0035 g/1 g; METHYLPARABEN SODIUM 0.0014 g/1 g; TITANIUM DIOXIDE 0.0073 g/1 g; PETROLATUM 0.142 g/1 g; PHENYLETHYL ALCOHOL 0.00215 g/1 g; GLYCERIN 0.0535 g/1 g

BM Pimples Cure Cream

Active ingredients (Ref. stand.)
Each 40gm contains
Berb. aquifol Ø 0.93 gm (HPUS)
Hydrocotyle Ø 0.93 gm (EHPI)
Kali brom Ø 0.18 gm (HPUS)

INACTIVE INGREDIENT

Purified water

Phenyl ethyl alcohol

Triethanolamine

Glycerine

Bee wax

Methyl paraben sodium

Propyl paraben sodium

Soft paraffin

Stearic acid

Talcum powder

Titanium dioxide

Indications:
(Derived from Materia Medica by W. Boericke, 1200 Remedies by R. Murphy, Materia Media by Blackwood & authentic homoeopathic references).
Help support to relieve the symptoms of acne and pimples, for detail please read the enclosed package (Product information leaflet).

PURPOSE

Indications:
(Derived from Materia Medica by W. Boericke, 1200 Remedies by R. Murphy, Materia Media by Blackwood & authentic homoeopathic references).
Help support to relieve the symptoms of acne and pimples, for detail please read the enclosed package (Product information leaflet).

DOSAGE AND ADMINISTRATION

please read the enclosed package (Product information leaflet).

CONTRAINDICATIONS

Care & contra-indications:
This is a homoeopathic product, no contra-indications are established.

WARNINGS

Precautions/storage:
Keep away from children and store at cool and dry place.

KEEP OUT OF REACH OF CHILDREN

Precautions/storage:
Keep away from children and store at cool and dry place.

Package 1: